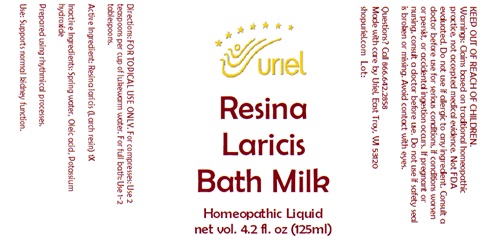 DRUG LABEL: Resina Laricis Bath Milk
NDC: 48951-8326 | Form: LIQUID
Manufacturer: Uriel Pharmacy Inc.
Category: homeopathic | Type: HUMAN OTC DRUG LABEL
Date: 20251107

ACTIVE INGREDIENTS: LARIX DECIDUA RESIN 1 [hp_X]/1 mL
INACTIVE INGREDIENTS: WATER; OLEIC ACID; POTASSIUM HYDROXIDE

Resina Laricis Bath Milk

INDICATIONS AND USAGE

Directions: FOR TOPICAL USE ONLY.

DOSAGE AND ADMINISTRATION

For compresses: Use 2 teaspoons per cup of lukewarm water. For full bath: Use 1-2 tablespoons.

Active Ingredient: Resina laricis (Larch resin) 1X

Inactive Ingredients: Spring water, Oleic acid, Potassium hydroxide

Prepared using rhythmical processes.

PURPOSE

Use: Supports normal kidney function.

KEEP OUT OF REACH OF CHILDREN.

WARNINGS

Warnings: Claims based on traditional homeopathic practice, not accepted medical evidence. Not FDA evaluated. Do not use if allergic to any ingredient. Consult a doctor before use for serious conditions, if conditions worsen or persist, or accidental ingestion occurs. If pregnant or nursing, consult a doctor before use. Do not use if safety seal is broken or missing. Avoid contact with eyes.

Questions? Call 866.642.2858
Made with care by Uriel, East Troy, WI 53120
shopuriel.com